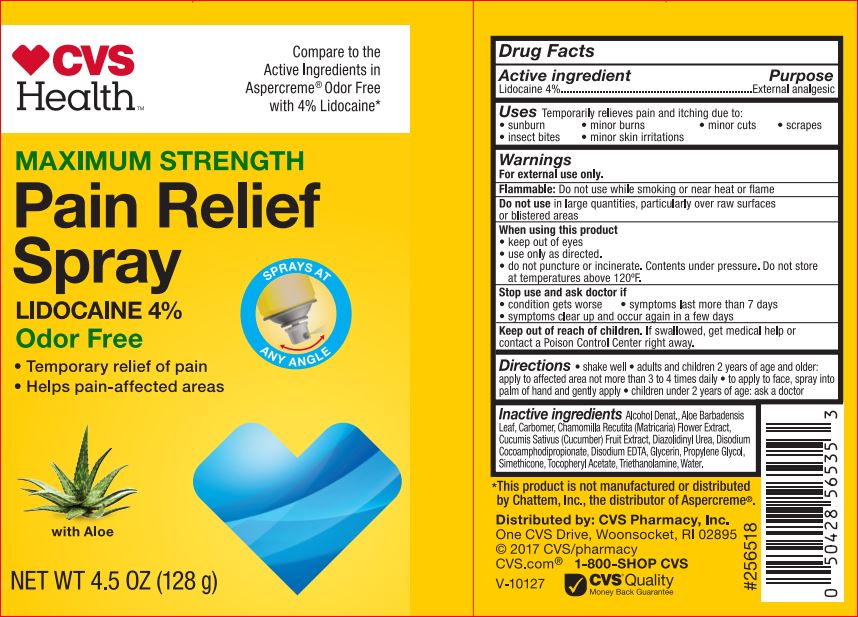 DRUG LABEL: Pain Relief
NDC: 69842-049 | Form: LIQUID
Manufacturer: CVS
Category: otc | Type: HUMAN OTC DRUG LABEL
Date: 20171220

ACTIVE INGREDIENTS: Lidocaine 4 g/100 mL
INACTIVE INGREDIENTS: Alcohol; ALOE VERA LEAF; CHAMOMILE; CUCUMBER; Diazolidinyl Urea; Disodium Cocoamphodipropionate; EDETATE DISODIUM; Glycerin; Propylene Glycol; .ALPHA.-TOCOPHEROL ACETATE; TROLAMINE; Water

Drug Facts

Active ingredient Purpose
Lidocaine 4%................................................................External analgesic

Uses

Temporarily relieves pain and itching due to: • sunburn • minor burns • minor cuts • scrapes • insect bites • minor skin irritations

Warnings For external use only.

Flammable: Do not use while smoking or near heat or flame Do not use in large quantities, particularly over raw surfaces or blistered areas
When using this product
• keep out of eyes
• use only as directed.
• do not puncture or incinerate. Contents under pressure. Do not store at temperatures above 120ºF.
Stop use and ask doctor if
• condition gets worse • symptoms last more than 7 days
• symptoms clear up and occur again in a few days

Keep out of reach of children. If swallowed, get medical help or contact a Poison Control Center right away

DOSAGE AND ADMINISTRATION

Directions • shake well • adults and children 2 years of age and older: apply to affected area not more than 3 to 4 times daily • children under 2 years of age: ask a doctor • to apply to face, spray into palm of hand and gently apply

Inactive ingredients

Aloe Barbadensis Leaf Juice, SD Alcohol 40, Propylene Glycol, Glycerin,
Simethicone, Tocopheryl Acetate, Triethanolamine, Carbomer,
Diazolidinyl Urea, Methylparaben, Propylparaben, Disodium
Cocoamphodipropionate, Disodium EDTA